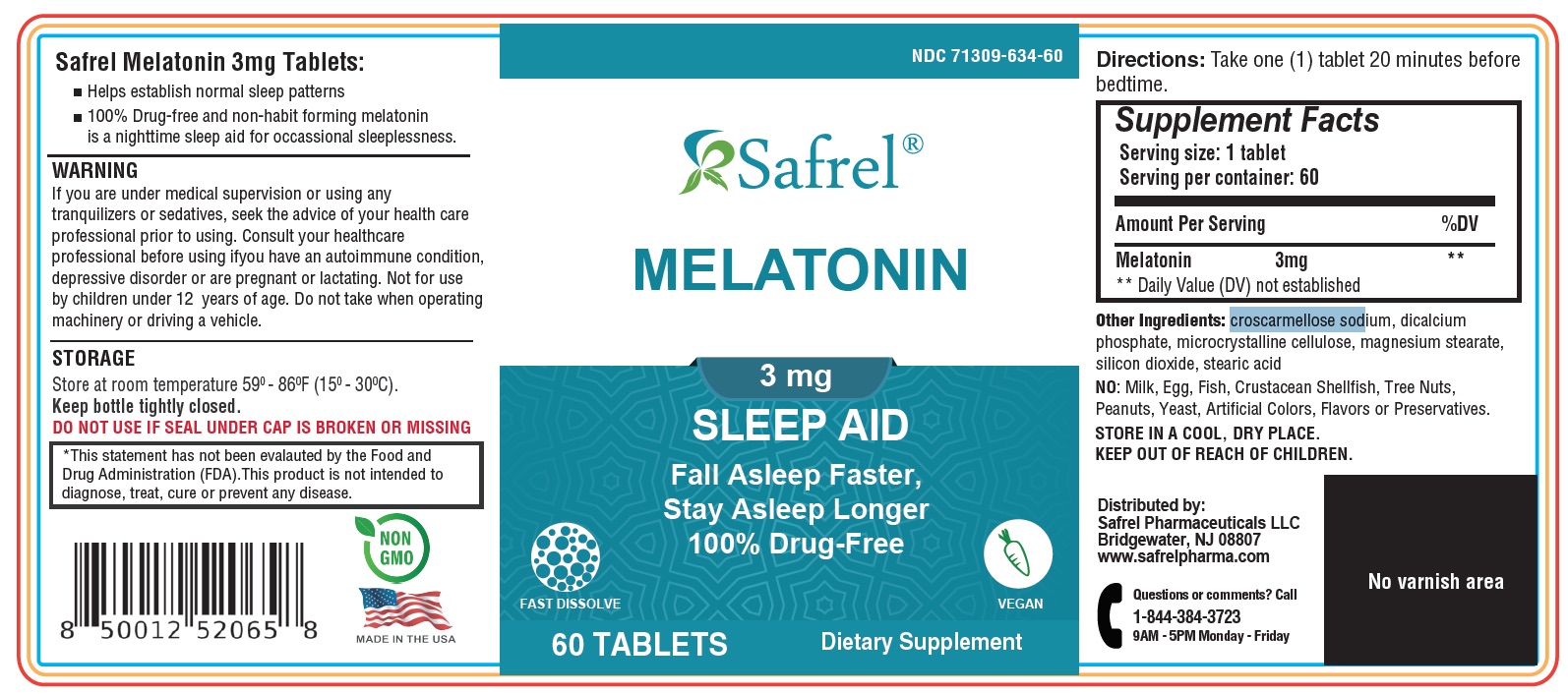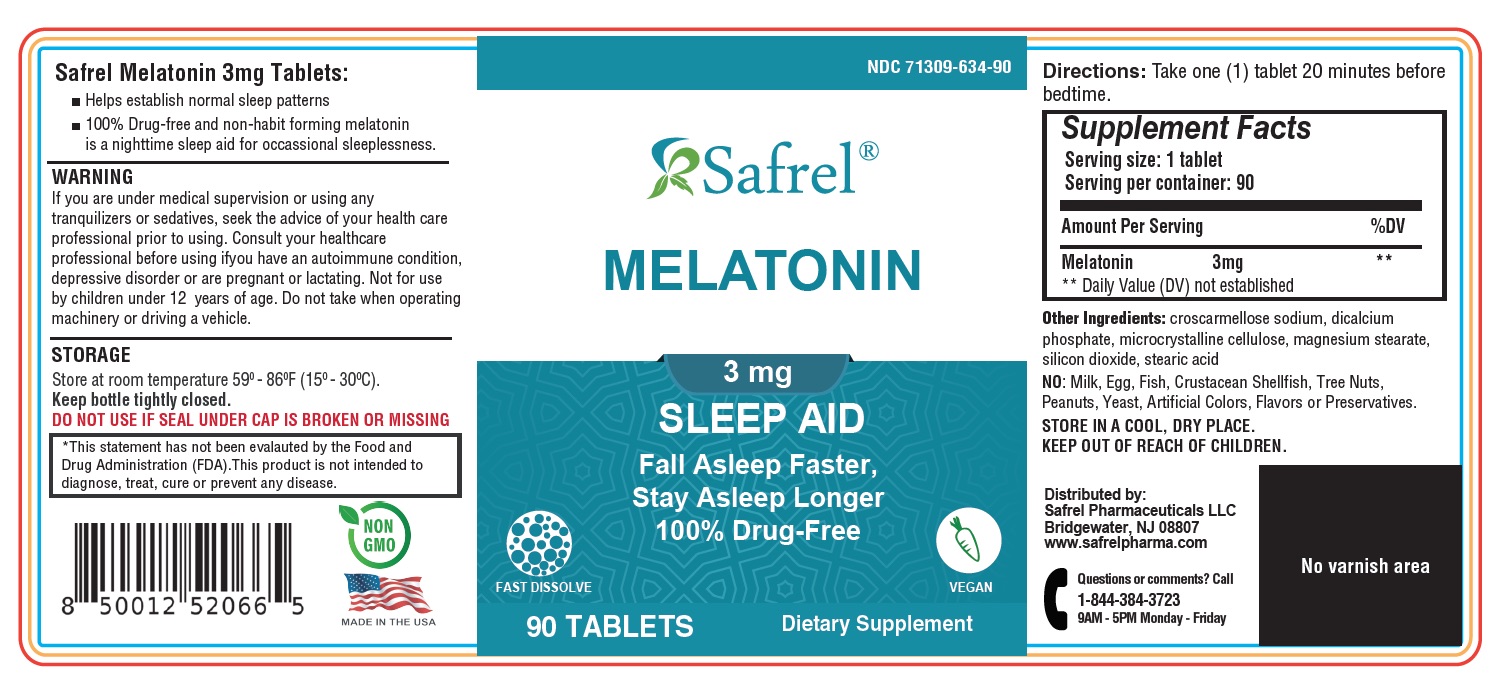 DRUG LABEL: Safrel Melatonin
NDC: 71309-634 | Form: TABLET
Manufacturer: Safrel Pharmaceuticals, LLC.
Category: other | Type: DIETARY SUPPLEMENT
Date: 20200830

ACTIVE INGREDIENTS: Melatonin 3 mg/1 1
INACTIVE INGREDIENTS: CROSCARMELLOSE SODIUM; DIBASIC CALCIUM PHOSPHATE DIHYDRATE; SILICON DIOXIDE; STEARIC ACID; MAGNESIUM STEARATE; MICROCRYSTALLINE CELLULOSE

Melatonin Tablets 3 mg

STATEMENT OF IDENTITY

SUPPLEMENT FACTS

Suggested Use: For adults, chew two gummies 30 minutes prior to sleep event. Gummy should be chewed before swallowing.

Serving Size: 2 gummies

Servings Per Container: 30

Amount per serving

%Daily Value

Melatonin

3mg

**

** Daily Value (DV) not established

Other ingredients: croscarmellose sodium, dicalcium phosphate, microcrystalline cellulose, magnesium stearate, silicon dioxide, stearic acid

HEALTH CLAIM

NO: Milk, Egg, Fish, Crustacean Shellfish, Tree Nuts, Peanuts, Yeast, Artificial Colors, Flavors or Preservatives.

Do not use if tamper-evident seal is broken or missing. Store at room temperature 590 - 860F (150 - 300C). Keep out of reach of children. If pregnant, breast-feeding or taking any medications, consult a physician before use. Discontinue use and consult a physician, if adverse reactions occur.

HEALTH CLAIM

*This statement has not been evaluated by the Food and Drug Administration. This product is not intended to diagnose, treat, cure, or prevent any disease.

HEALTH CLAIM

Distributed by:

Safrel Pharmaceuticals LLC

Bridgewater, NJ 08807

www.safrelpharma.com

Questions or comments?

Call 1-844-384-3723

9AM - 5PM Monday - Friday

WARNING

If you are under medical supervision or using any tranquilizers or sedatives, seek the advice of your health care professional prior to using. Consult your healthcare professional before using ifyou have an autoimmune condition, depressive disorder or are pregnant or lactating. Not for use by children under 12 years of age. Do not take when operating machinery or driving a vehicle.

PRINCIPAL DISPLAY PANEL - Vitamin Bottle Label

Safrel Melatonin 3mg Tablets:

Helps establish normal sleep patterns 100%
Drug-free and non-habit forming melatonin is a nighttime sleep aid for occassional sleeplessness.
Vegan
Fast Dissolve

DIETARY SUPPLEMENT

Melatonin 3mg Tablets 60 Count

Melatonin 3mg Tablets 90 count